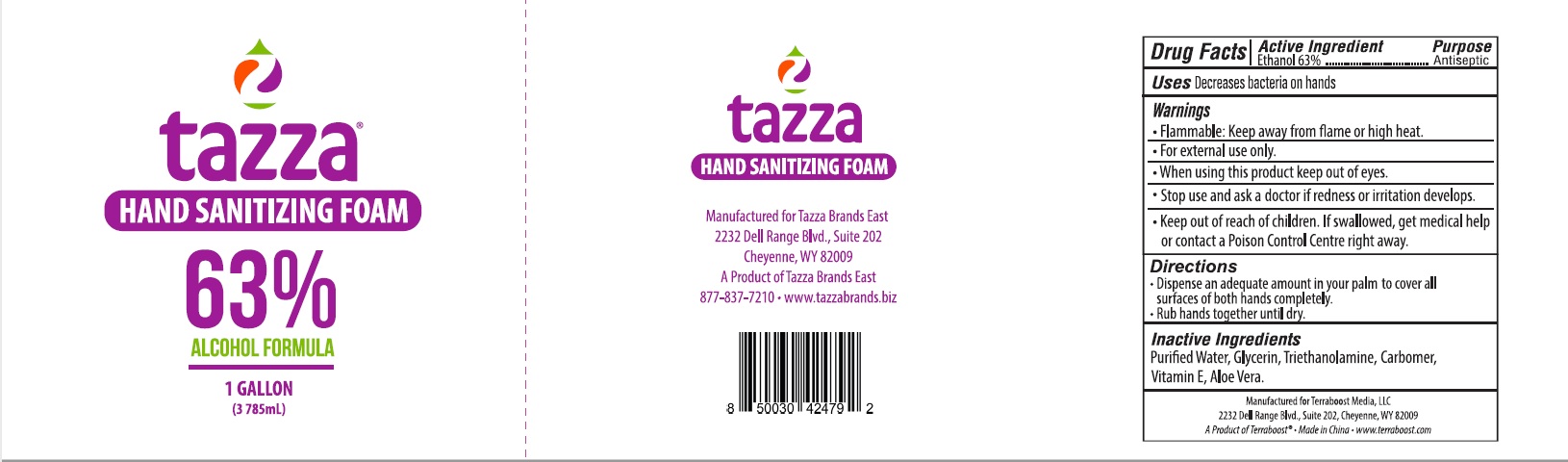 DRUG LABEL: tazza hand sanitizing foam
NDC: 76370-0022 | Form: LIQUID
Manufacturer: Tazza Brands East Inc.
Category: otc | Type: HUMAN OTC DRUG LABEL
Date: 20240125

ACTIVE INGREDIENTS: ALCOHOL 63 mL/100 mL
INACTIVE INGREDIENTS: WATER; ALOE VERA LEAF; .ALPHA.-TOCOPHEROL; GLYCERIN; TROLAMINE; CARBOMER HOMOPOLYMER, UNSPECIFIED TYPE

tazza hand sanitizing foam 63%

Active ingredient

Ethanol 63%

Purpose

Antiseptic

Uses

Decreases bacteria on hands

Warnings

Flammable: Keep away from flame or high heat.

For external use only.

When using this product keep out of eyes.

Stop use and ask a doctor if redness or irritation develops.

Keep out of reach of children. If swallowed, get medical help or contact a Poison Control Centre right away.

Directions

- Dispense an adequate amount in your palm to cover all surfaces of both hands completely.
- Rub hands together until dry.

Inactive ingredients

Purified water, glycerin, triethanolamine, carbomer, vitamin E, aloe vera.

Manufactured for Terraboost Media, LLC
2232 Dell Range Blvd., Suite 202, Cheyenne, WY 82009
A Product of Terraboost® • Made in China • www.terraboost.com

PACKAGE LABEL

tazza

HAND SANITIZING FOAM

63%

ALCOHOL FORMULA

1 GALLON (3785 mL)

Manufactured for Tazza Brands East
2232 Dell Range Blvd., Suite 202
Cheyenne, WY 82009
A Product of Tazza Brands East
877-837-7210 • www.tazzabrands.biz